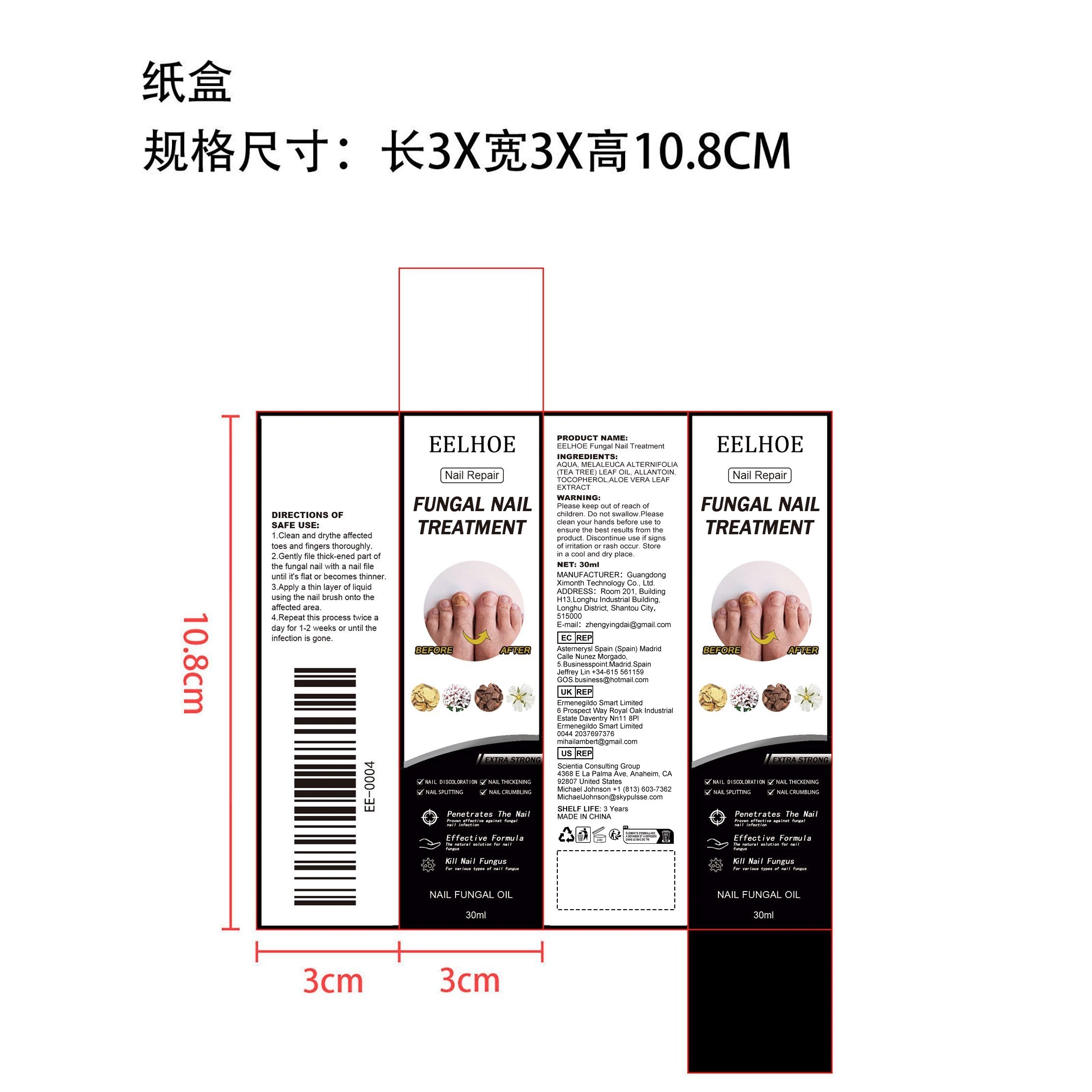 DRUG LABEL: EELHOE Fungal Nail Treatment
NDC: 84660-037 | Form: LIQUID
Manufacturer: Guangdong Ximonth Technology Co., Ltd.
Category: otc | Type: HUMAN OTC DRUG LABEL
Date: 20240926

ACTIVE INGREDIENTS: TEA TREE OIL 7.5 mg/30 mg; ALLANTOIN 6 mg/30 mg; ALOE VERA LEAF 3 mg/30 mg; TOCOPHEROL 4.5 mg/30 mg
INACTIVE INGREDIENTS: WATER 9 mL/30 mg

Active Ingredient(s)

MELALEUCA ALTERNIFOLIA (TEA TREE) LEAF OIL、ALLANTOIN、TOCOPHEROL、ALOE VERA LEAF EXTRACT

Purpose

Repair Nail

Warnings

Please keep out of reach of children.Do not swallow.Please clean your hands before use to ensure the best results from the product.Discontinue use if signs of irritation or rash occur.Store in a cool and dry place.

Use

1.Clean and drythe affected toes and fingers thoroughly.
2.Gently file thick-ened part of the fungal nail with a nail file until it's flat or becomes thinner.
3.Apply a thin layer of liquid using the nail brush onto the affected area.
4.Repeat this process twice a day for 1-2 weeks or until the infection is gone.

STORAGE AND HANDLING

Avoid freezing and excessive heat above 40C (104F) ）
Store in a cool and dry place.

Do not use

Discontinue use if signs of irritation or rash occur.

STOP USE

Discontinue use if signs of irritation or rash occur.

KEEP OUT OF REACH OF CHILDREN

Please keep out of reach of children. Do not swallow.

INACTIVE INGREDIENT

AQUA